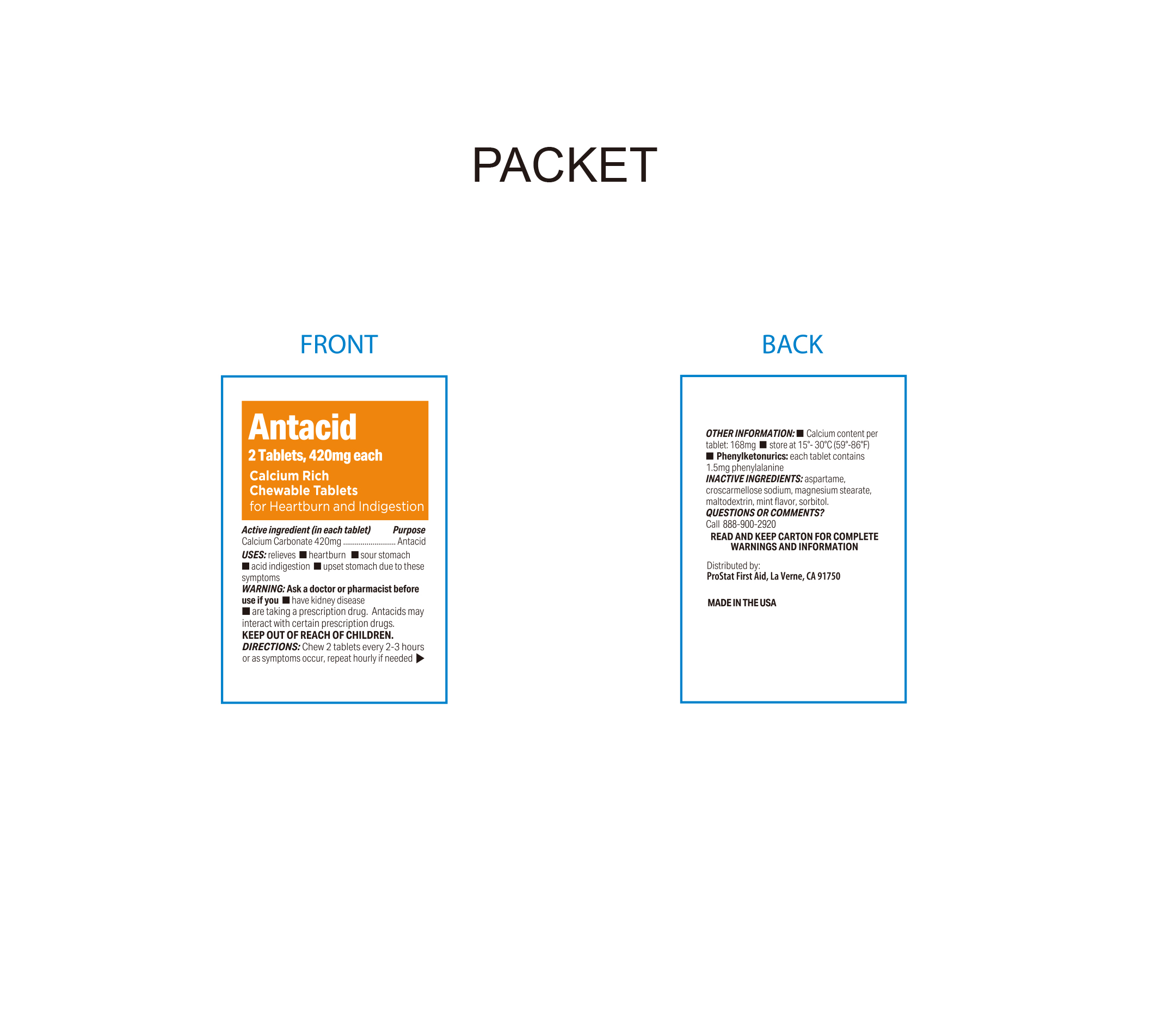 DRUG LABEL: Antacid
NDC: 58228-0091 | Form: TABLET
Manufacturer: ProStat First Aid
Category: otc | Type: HUMAN OTC DRUG LABEL
Date: 20250806

ACTIVE INGREDIENTS: CALCIUM CARBONATE 420 mg/1 1
INACTIVE INGREDIENTS: ASPARTAME; MAGNESIUM STEARATE; SORBITOL; CROSCARMELLOSE SODIUM; MALTODEXTRIN; MINT

ProStat Antacid Calcium Rich Chewable Tablets

Active Ingredient (in each tablet)

Calcium Carbonate 420mg

Purpose

Antacid

Uses

Relieves

- Heartburn
- sour stomach
- acid indigestion
- upset stomach due to these symptoms

Directions

Chew 2 tablets every 2-3 hours or as symptoms occur, repeat hourly if needed.

Ask a doctor or pharmacist before use if you

- have kidney disease
- are taking a prescription drug
- Antacids may interact with certain prescription drugs

Keep out of reach of children

Other Information

- Store at 15ºC - 30ºC (59ºF - 86ºF)
- Calcium content per tablet: 168mg
- Phenylketonurics: each tablet contains 1.5mg phenylalanine

Do not use if packet is open or torn

Tamper Evident

Chewable

Inactive Ingredients

Magnesium Stearate, Aspartame. Croscarmellose Sodium, Maltodextrin, mint flavor, sorbitol

Questions or Comments?

Call 1-888-900-2920

When using this product

Do not take more than 19 tablets in a 24 hour period or use the maximum dosage of this product for more than two weeks except under the advice and supervision of a doctor. If symptoms persist for more than two weeks, stop using this product and see a doctor.

Distributed By:

ProStat First Aid

La Verne, CA. 91750, USA

1-888-900-2920

*This product is not manufactured or distributed by GSK, owner of the registered trademark Tums®